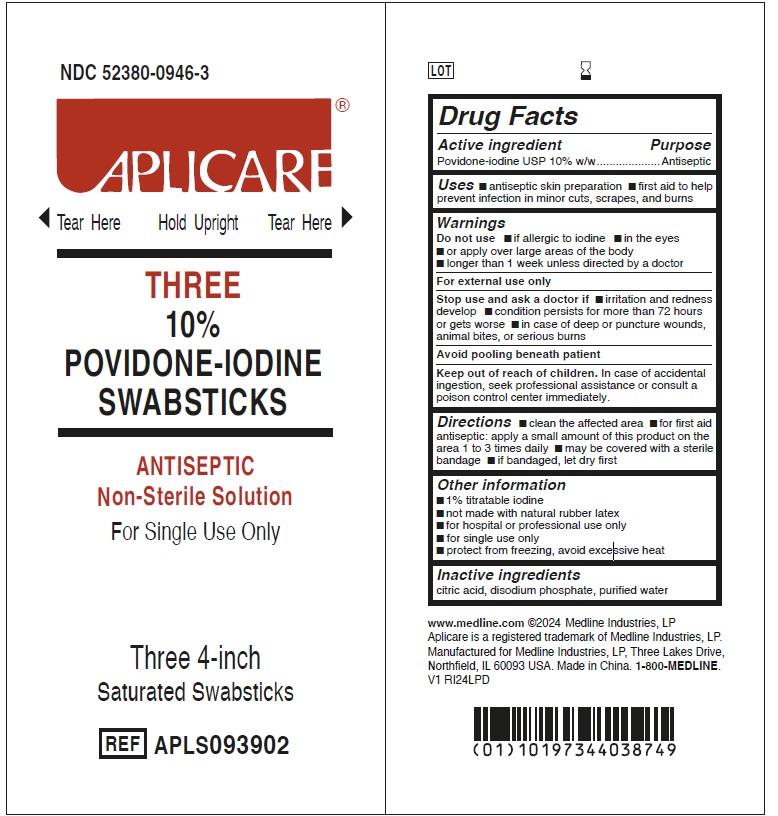 DRUG LABEL: Aplicare
NDC: 52380-0946 | Form: SWAB
Manufacturer: Aplicare Products LLC
Category: otc | Type: HUMAN OTC DRUG LABEL
Date: 20251218

ACTIVE INGREDIENTS: POVIDONE-IODINE 10 mg/1 g
INACTIVE INGREDIENTS: CITRIC ACID MONOHYDRATE; WATER; SODIUM PHOSPHATE, DIBASIC, ANHYDROUS

0946 Aplicare 10% Povidone-iodine Swabsticks

Active ingredient

Povidone-iodine USP 10% w/w

Purpose

Antiseptic

Uses

- antiseptic skin preparation
- first aid to help prevent infection in minor cuts, scrapes, and burns

Warnings

Do not use

- if allergic to iodine
- in the eyes
- or apply over large areas of the body
- longer than 1 week unless directed by a doctor

For external use only

Stop use and ask a doctor if

- irritation and redness develop
- condition persists for more than 72 hours or gets worse
- in case of deep or puncture wounds, animal bites, or serious burns

Avoid pooling beneath patient

Keep out of reach of children.

In case of accidental ingestion, seek professional assistance or consult a poison control center immediately.

Directions

- clean the affected area
- for first aid antiseptic: apply a small amount of this product on the area 1 to 3 times daily
- may be covered with a sterile bandage
- if bandaged, let dry first

Other information

- 1% titratable iodine
- not made with natural rubber latex
- for hospital or professional use only
- for single use only
- protect from freezing, avoid excessive heat

Inactive ingredients

citric acid, disodium phosphate, purified water

Manufacturer information

www.medline.com ©2024 Medline Industries, LP
Aplicare is a registered trademark of Medline Industries, LP.
Manufactured for Medline Industries, LP, Three Lakes Drive,
Northfield, IL 60093 USA. Made in China. 1-800-MEDLINE.
V1 RI24LPD